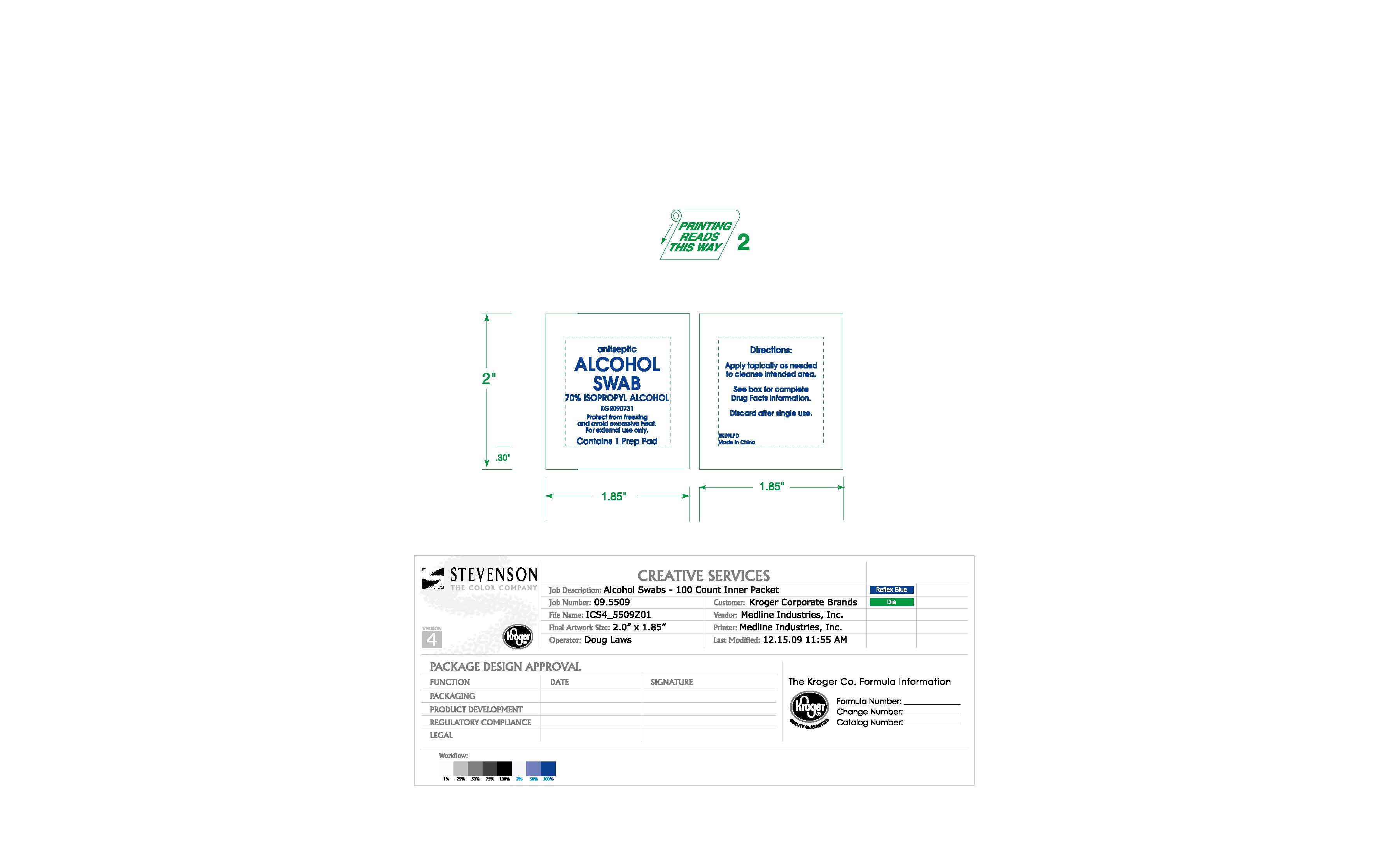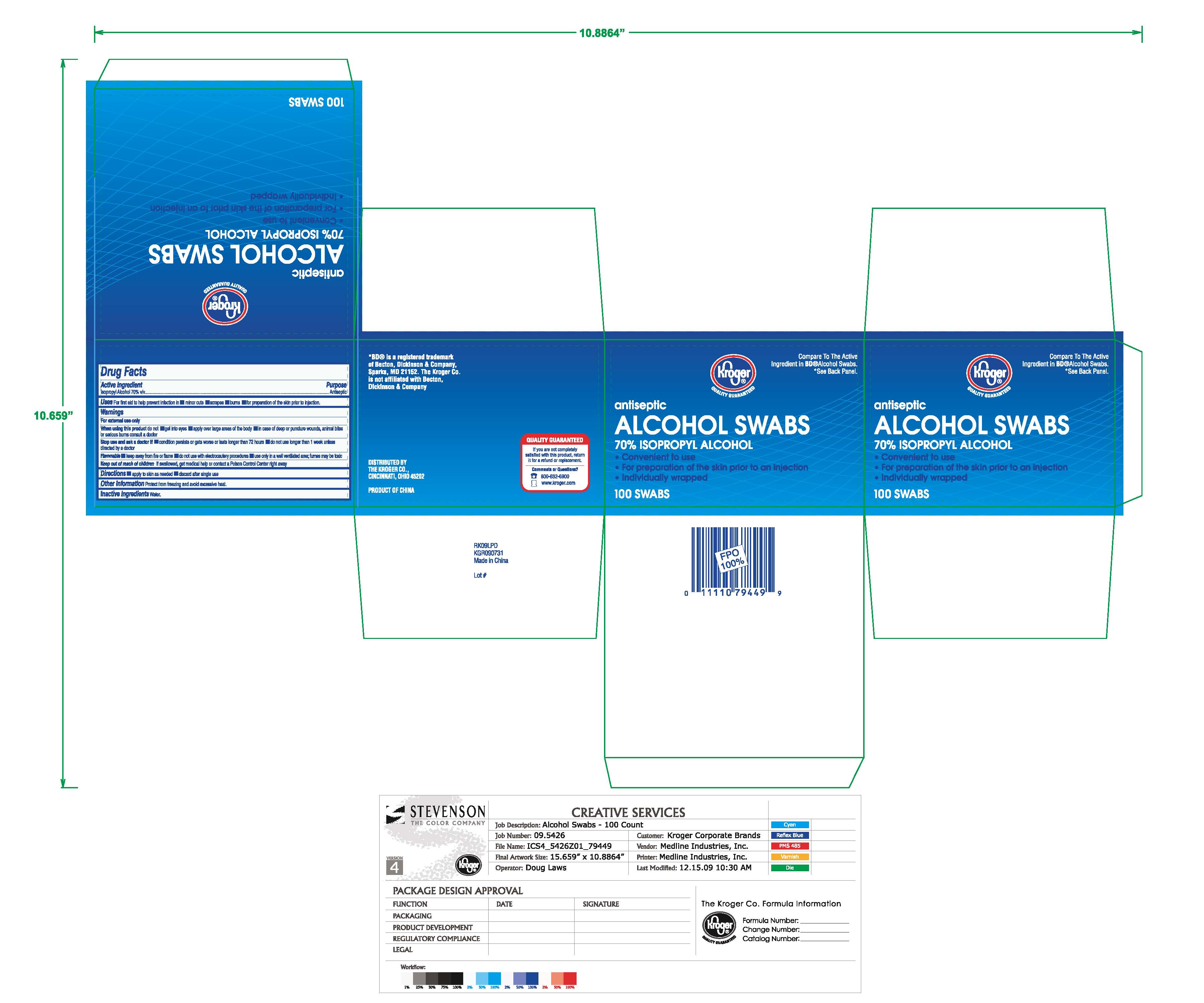 DRUG LABEL: Isopropyl Alcohol
NDC: 30142-809 | Form: SWAB
Manufacturer: The Kroger Company
Category: otc | Type: HUMAN OTC DRUG LABEL
Date: 20100331

ACTIVE INGREDIENTS: Isopropyl Alcohol 70 mL/1 1

Drug Facts

Active ingredient

Isopropyl Alcohol 70%

Purpose

Antiseptic

Uses

For preparation of the skin prior to injection. For first aid to decrease germs in minor cuts, scrapes and burns.

Warnings

- For external use only.
- Flammable. Keep away from fire or flame.
- Use only in a well-ventilated area; fumes may be toxic.

Do not use

- with electrocautery procedures
- longer than 1 week unless directed by a doctor

When using this product do not

- get into eyes
- apply over large areas of the body

In case of deep or puncture wounds, animal bites or serious burns, consult a doctor.

Stop use and ask a doctor if

- condition persists or gets worse or lasts for more than 72 hours

Keep out of reach of children

If swallowed, get medical help or contact a Poison Control center right away.

Directions

- Wipe injection site vigorously
- Apply to skin as needed
- Discard after single use

Storage

Protect from freezing. Avoid excessive heat.

Inactive Ingredients

Water

Questions

1-800-MEDLINE

Principal Display Panel

Alcohol Prep Pads

For external use only